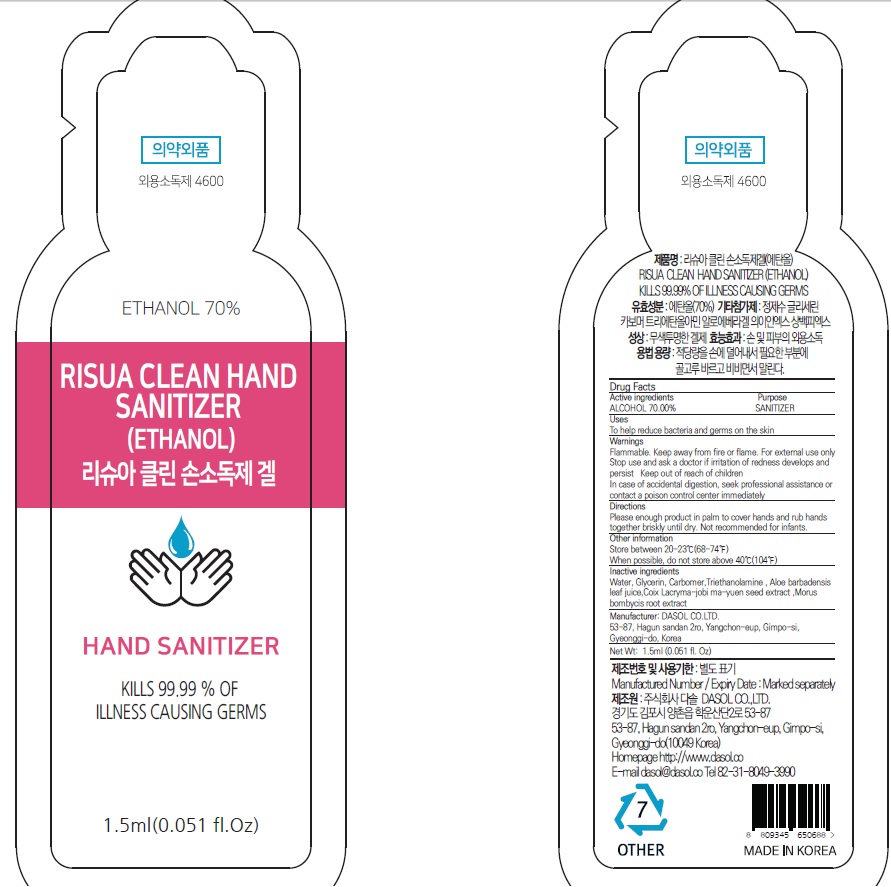 DRUG LABEL: RISUA CLEAN HAND SANITIZER ETHANOL
NDC: 73758-030 | Form: GEL
Manufacturer: Dasol Co.,ltd.
Category: otc | Type: HUMAN OTC DRUG LABEL
Date: 20200428

ACTIVE INGREDIENTS: ALCOHOL 70.0 g/100 mL
INACTIVE INGREDIENTS: Water; Glycerin; CARBOMER HOMOPOLYMER, UNSPECIFIED TYPE; TROLAMINE; ALOE VERA LEAF

Active Ingredients

Active ingredients: ALCOHOL 70.00%

INACTIVE INGREDIENT

Inactive ingredients:

Water, Glycerin, Carbomer, Triethanolamine, Aloe barbadensis leaf juice, Coix Lacryma-jobi ma-yuen seed extract, Morus bombycis root extract

Purpose

Purpose: SANITIZER

Warnings

Flammable. Keep away from fire or flame.
For external use only
Stop use and ask a doctor if irritation of redness develops and persist
Keep out of reach of children
In case of accidental digestion, seek professional assistance or contact a poison control center immediately

KEEP OUT OF REACH OF CHILDREN

Uses

To help remove bacteria and germs on the skin

Directions

Please enough product in palm to cover hands and rub hands together briskly until dry.
Not recommended for infants.

Other information

Store between 20-23℃(68-74℉)
When possible, do not store above 40℃(104℉)